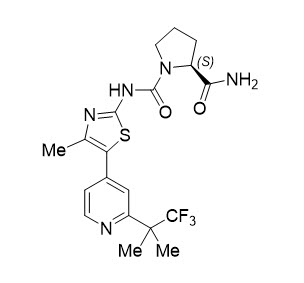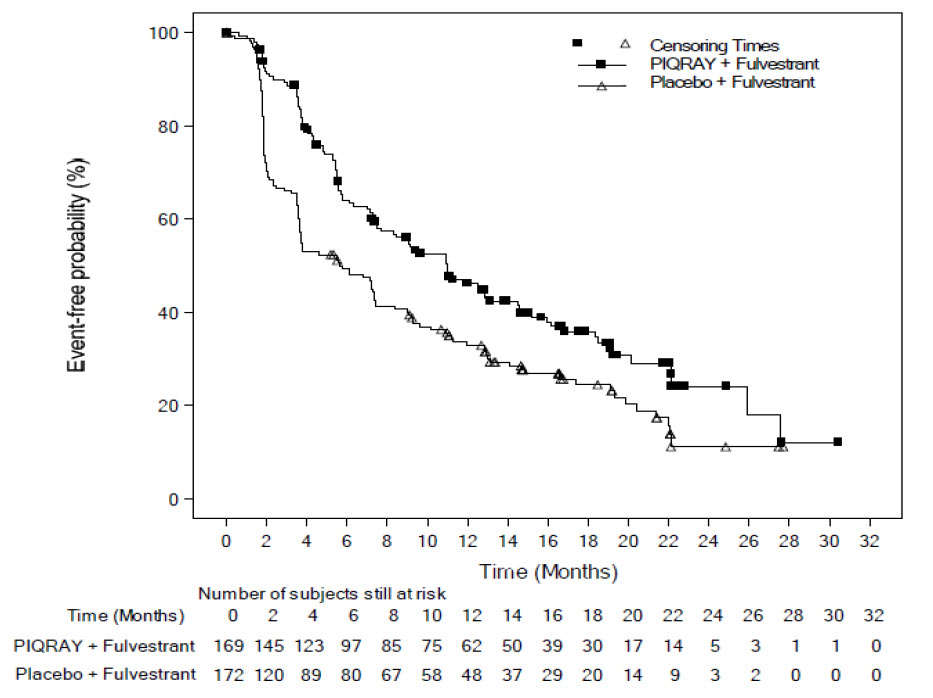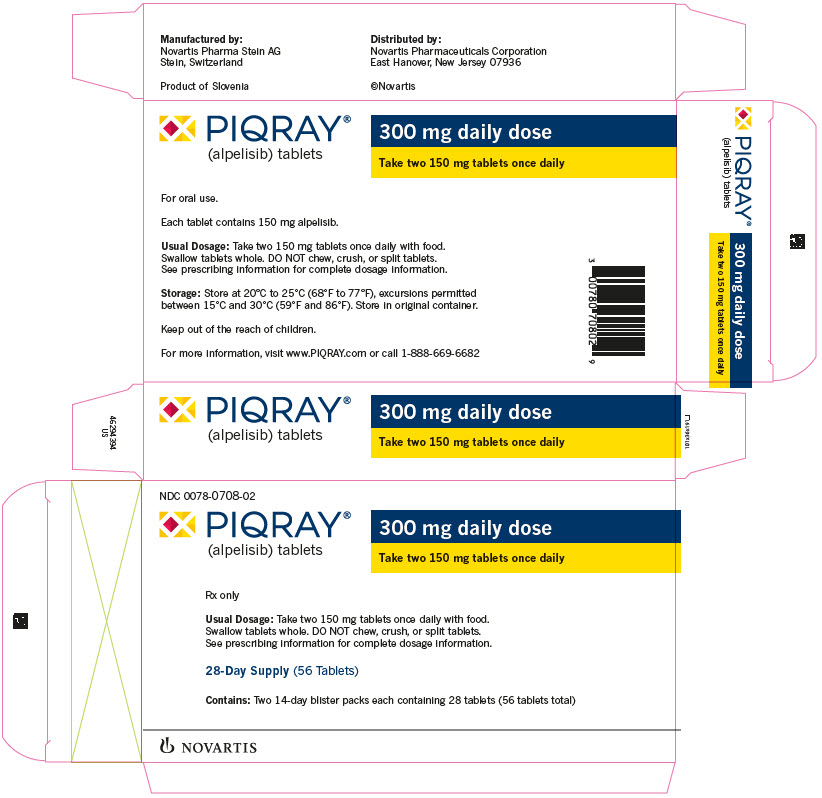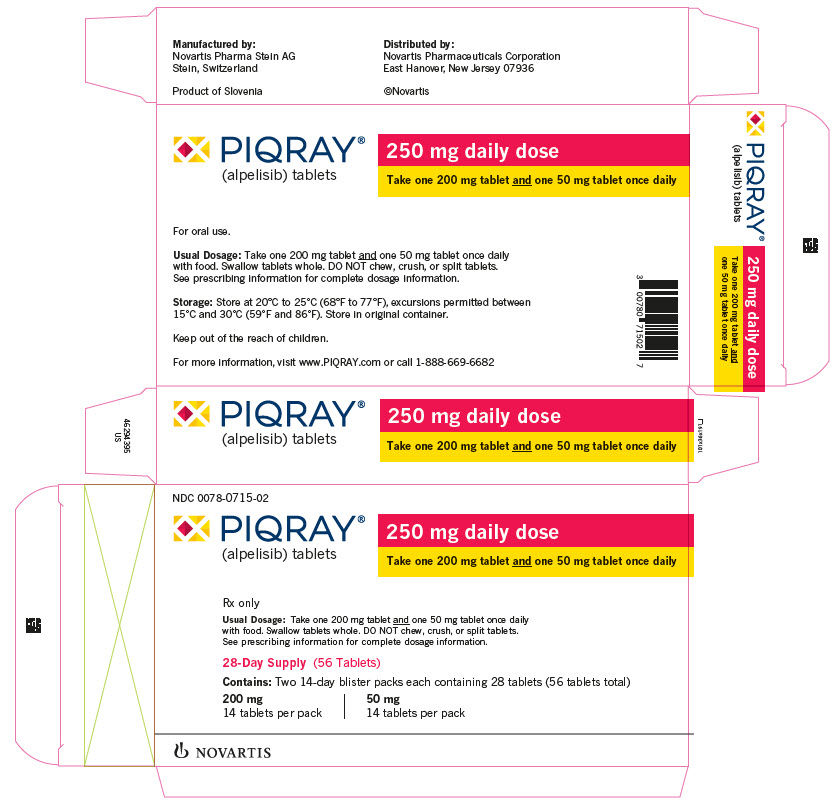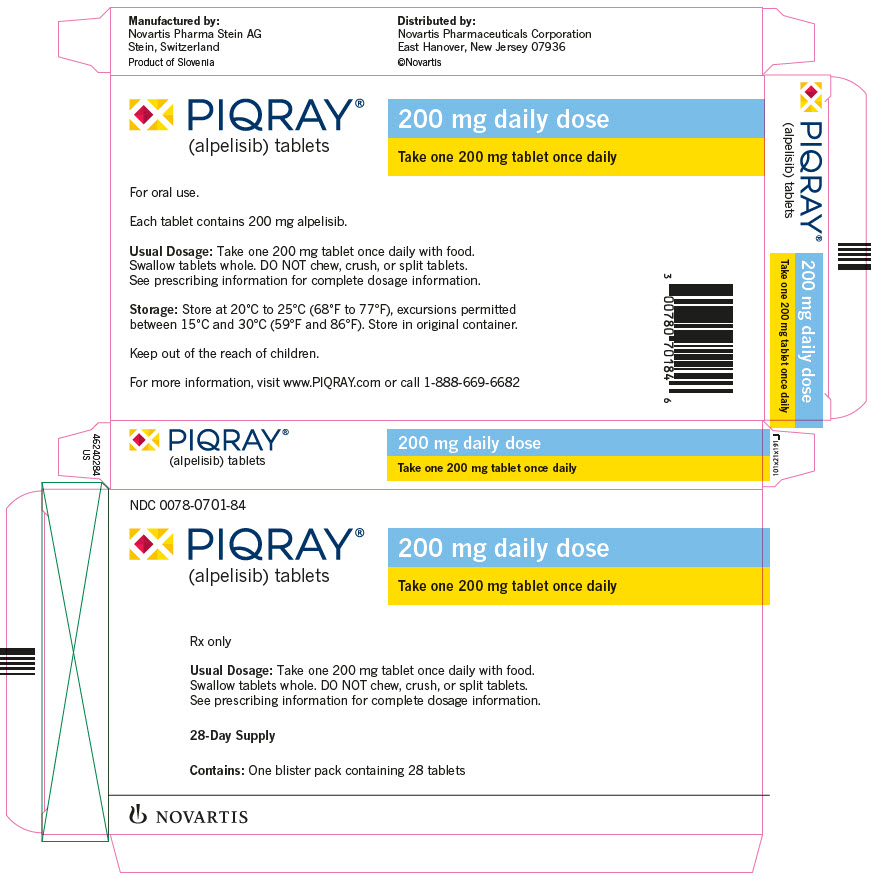 DRUG LABEL: PIQRAY
NDC: 0078-0708 | Form: TABLET
Manufacturer: Novartis Pharmaceuticals Corporation
Category: prescription | Type: HUMAN PRESCRIPTION DRUG LABEL
Date: 20251215

ACTIVE INGREDIENTS: ALPELISIB 150 mg/1 1
INACTIVE INGREDIENTS: CELLULOSE, MICROCRYSTALLINE; MANNITOL; SODIUM STARCH GLYCOLATE TYPE A POTATO; HYPROMELLOSE, UNSPECIFIED; MAGNESIUM STEARATE; TALC; POLYETHYLENE GLYCOL 4000; TITANIUM DIOXIDE; FERRIC OXIDE RED; FERROSOFERRIC OXIDE

HIGHLIGHTS OF PRESCRIBING INFORMATION

These highlights do not include all the information needed to use PIQRAY safely and effectively. See full prescribing information for PIQRAY.
PIQRAY® (alpelisib) tablets, for oral use
Initial U.S. Approval: 2019

RECENT MAJOR CHANGES

Indications and Usage (1) | 1/2024
Dosage and Administration, Dose Modifications for Adverse Reactions (2.3) | 1/2024
Warnings and Precautions, Hyperglycemia (5.3) | 1/2024

1 INDICATIONS AND USAGE

PIQRAY is a kinase inhibitor indicated in combination with fulvestrant for the treatment of adults with hormone receptor (HR)-positive, human epidermal growth factor receptor 2 (HER2)-negative, PIK3CA-mutated, advanced or metastatic breast cancer as detected by an FDA-approved test following progression on or after an endocrine-based regimen.

2 DOSAGE AND ADMINISTRATION

- Recommended Dose: 300 mg (two 150 mg tablets) taken orally once daily with food. (2.2)
- For adverse reactions, consider dose interruption, dose reduction, or discontinuation. (2.3)

3 DOSAGE FORMS AND STRENGTHS

Tablets: 50 mg, 150 mg, and 200 mg

4 CONTRAINDICATIONS

Severe hypersensitivity to PIQRAY or to any of its components. (4)

5 WARNINGS AND PRECAUTIONS

- Severe Hypersensitivity: Permanently discontinue PIQRAY. Promptly initiate appropriate treatment. (5.1)
- Severe Cutaneous Adverse Reactions (SCARs): PIQRAY can cause SCARs, including Stevens-Johnson syndrome (SJS), erythema multiforme (EM), toxic epidermal necrolysis (TEN), and drug reaction with eosinophilia and systemic symptoms (DRESS). Interrupt PIQRAY for signs or symptoms of SCARs. Permanently discontinue PIQRAY if SCARs are confirmed. (5.2)
- Hyperglycemia: PIQRAY can cause severe hyperglycemia, in some cases associated with hyperglycemic hyperosmolar non-ketotic syndrome (HHNKS) or ketoacidosis. Before initiating treatment with PIQRAY, test fasting plasma glucose (FPG), HbA1c, and optimize blood glucose. Consider premedication with metformin prior to the initiation of PIQRAY based on patient risk factors for hyperglycemia, gastrointestinal tolerability, and clinical situation. Use of metformin premedication prior to the initiation of PIQRAY decreases the incidence and severity of hyperglycemia, but increases the incidence and severity of nausea, vomiting, and diarrhea adverse reactions. After initiating treatment, monitor FPG and HbA1c periodically. Initiate or optimize anti-hyperglycemic medications as clinically indicated. Interrupt, reduce dose, or discontinue PIQRAY if severe hyperglycemia occurs. (2.3, 5.3, 6.1)
- Pneumonitis: PIQRAY can cause severe pneumonitis and interstitial lung disease. Monitor for clinical symptoms or radiological changes. Interrupt or discontinue PIQRAY if severe pneumonitis occurs. (2.3, 5.4)
- Diarrhea or Colitis: PIQRAY causes diarrhea in most patients and may be severe, resulting in dehydration and acute kidney injury. Advise patients to start antidiarrheal treatment, increase oral fluids, and notify their healthcare provider if diarrhea occurs.
  Colitis has been reported in patients treated with PIQRAY. Monitor for diarrhea and additional symptoms of colitis, including abdominal pain and mucus or blood in stool.
  Interrupt, reduce dose, or discontinue PIQRAY if severe diarrhea or colitis occurs. Patients with colitis may require additional treatment, such as enteric-acting and/or systemic steroids. (2.3, 5.5, 6.2)
- Embryo-Fetal Toxicity: PIQRAY can cause fetal harm. Advise patients of potential risk to a fetus and to use effective contraception. (5.6, 8.1, 8.3)
  Refer to the Full Prescribing Information of fulvestrant for pregnancy and contraception information.

6 ADVERSE REACTIONS

Most common adverse reactions, including laboratory abnormalities (all Grades, incidence ≥ 20%) were glucose increased, creatinine increased, diarrhea, rash, lymphocyte count decreased, gamma-glutamyl transferase (GGT) increased, nausea, alanine aminotransferase (ALT) increased, fatigue, hemoglobin decreased, lipase increased, decreased appetite, stomatitis, vomiting, weight decreased, calcium decreased, glucose decreased, activated partial thromboplastin time (aPTT) prolonged, and alopecia. (6.1)

To report SUSPECTED ADVERSE REACTIONS, contact Novartis Pharmaceuticals Corporation at 1-888-669-6682 or FDA at 1-800-FDA-1088 or www.fda.gov/medwatch.

7 DRUG INTERACTIONS

- CYP3A4 Inducers: Avoid coadministration of PIQRAY with a strong CYP3A4 inducer. Consider an alternative concomitant drug with no or minimal potential to induce CYP3A4. (7.1)
- Breast Cancer Resistance Protein (BCRP) Inhibitors: Avoid the use of BCRP inhibitors in patients treated with PIQRAY. If unable to use alternative drugs, closely monitor for increased adverse reactions. (7.1)

8 USE IN SPECIFIC POPULATIONS

Lactation: Advise not to breastfeed. (8.2)

FULL PRESCRIBING INFORMATION

1 INDICATIONS AND USAGE

PIQRAY is indicated in combination with fulvestrant for the treatment of adults with hormone receptor (HR)-positive, human epidermal growth factor receptor 2 (HER2)-negative, PIK3CA-mutated, advanced or metastatic breast cancer as detected by an FDA-approved test following progression on or after an endocrine-based regimen.

2 DOSAGE AND ADMINISTRATION

2.1 Patient Selection

Select patients for the treatment of HR-positive, HER2-negative advanced or metastatic breast cancer with PIQRAY, based on the presence of one or more PIK3CA mutations in tumor tissue or plasma specimens [see Clinical Studies (14)]. If no mutation is detected in a plasma specimen, test tumor tissue. Information on FDA-approved tests for the detection of PIK3CA mutations in breast cancer is available at: http://www.fda.gov/CompanionDiagnostics.

2.2 Dosage and Administration

The recommended dose of PIQRAY is 300 mg (two 150 mg film-coated tablets) taken orally, once daily, with food [see Clinical Pharmacology (12.3)].

Continue treatment until disease progression or unacceptable toxicity occurs [see Dosage and Administration (2.3)].

Patients should take their dose of PIQRAY at approximately the same time each day.

Swallow PIQRAY tablets whole (tablets should not be chewed, crushed or split prior to swallowing). No tablet should be ingested if it is broken, cracked, or otherwise not intact.

If a dose of PIQRAY is missed, it can be taken with food within 9 hours after the time it is usually taken. After more than 9 hours, skip the dose for that day. The next day, take PIQRAY at the usual time.

If the patient vomits after taking the dose, advise the patient not to take an additional dose on that day, and to resume the dosing schedule the next day at the usual time.

When given with PIQRAY, the recommended dose of fulvestrant is 500 mg administered on Days 1, 15, and 29, and once monthly thereafter. Refer to the Full Prescribing Information for fulvestrant.

2.3 Dose Modifications for Adverse Reactions

The recommended dose modifications for adverse reactions are listed in Table 1.

Table 1: PIQRAY Dose Reduction Guidelines for Adverse Reactions^1
PIQRAY dose level | Dose and schedule | Number and strength of tablets
Starting dose | 300 mg once daily | Two 150 mg tablets
First-dose reduction | 250 mg once daily | One 200 mg tablet and one 50 mg tablet
Second-dose reduction | 200 mg once daily^2 | One 200 mg tablet
^1Only one dose reduction is permitted for pancreatitis.
^2If further dose reduction below 200 mg once daily is required, discontinue PIQRAY.

Tables 2, 3, 4, and 5 summarize recommendations for dose interruption, reduction, or discontinuation of PIQRAY in the management of specific adverse reactions.

Cutaneous Adverse Reactions

If a severe cutaneous adverse reaction (SCAR) is confirmed, permanently discontinue PIQRAY. Do not reintroduce PIQRAY in patients who have experienced previous SCAR during PIQRAY treatment [see Warnings and Precautions (5.2)].

Table 2: Dose Modification and Management for Rash and Severe Cutaneous Adverse Reactions (SCARs)
[see Warnings and Precautions (5.1, 5.2)]
Grade^1,2 | Recommendation^3
Grade 1 (< 10% body surface area (BSA) with active skin toxicity) | No PIQRAY dose adjustment required. Initiate topical corticosteroid treatment. Consider adding oral antihistamine to manage symptoms. If active rash is not improved within 28 days of appropriate treatment, add a low dose systemic corticosteroid. If the etiology is SCAR, permanently discontinue PIQRAY.
Grade 2 (10%-30% BSA with active skin toxicity) | No PIQRAY dose adjustment required. Initiate or intensify topical corticosteroid and oral antihistamine treatment. Consider low dose systemic corticosteroid treatment. If rash improves to Grade ≤ 1 within 10 days, systemic corticosteroid may be discontinued. If the etiology is SCAR, permanently discontinue PIQRAY.
Grade 3 (e.g., severe rash not responsive to medical management) (> 30% BSA with active skin toxicity) | Interrupt PIQRAY. Initiate or intensify topical/systemic corticosteroid and oral antihistamine treatment. If the etiology is SCAR, permanently discontinue PIQRAY. If the etiology is not a SCAR, interrupt dose until improvement to Grade ≤ 1, then resume PIQRAY at next lower dose level.
Grade 4 (e.g., severe bullous, blistering or exfoliating skin conditions) (any % BSA associated with extensive superinfection, with IV antibiotics indicated; life-threatening consequences) | Permanently discontinue PIQRAY.
^1Grading according to Common Terminology Criteria for Adverse Events (CTCAE) Version 5.0.
^2For all grades of rash, consider consultation with a dermatologist.
^3Antihistamines administered prior to rash onset may decrease incidence and severity of rash based on the SOLAR-1 trial.

Hyperglycemia

Before initiating treatment with PIQRAY, test fasting plasma glucose (FPG), HbA1c, and optimize blood glucose.

Consider premedication with metformin prior to the initiation of PIQRAY in combination with fulvestrant based on patient risk factors for hyperglycemia, gastrointestinal tolerability, and clinical situation [see Warnings and Precautions (5.3) and Adverse Reactions (6.1)].

After initiating treatment with PIQRAY, monitor fasting glucose (FPG or fasting blood glucose) at least once every week for the first 2 weeks, then at least once every 4 weeks, and as clinically indicated. Monitor HbA1c every 3 months and as clinically indicated. In patients with risk factors for hyperglycemia, monitor fasting glucose more closely and as clinically indicated [see Warnings and Precautions (5.3)].

Table 3: Dose Modification and Management for Hyperglycemia
[see Warnings and Precautions (5.3)]
Fasting plasma glucose (FPG)/Fasting blood glucose values^1 | Recommendation
Dose modifications and management should only be based on fasting glucose values (FPG or fasting blood glucose).
Grade 1 Fasting glucose > ULN -160 mg/dL or > ULN -8.9 mmol/L | No PIQRAY dose adjustment required. Initiate or intensify anti-hyperglycemic treatment^2.
Grade 2 Fasting glucose > 160-250 mg/dL or > 8.9-13.9 mmol/L | No PIQRAY dose adjustment required. Initiate or intensify anti-hyperglycemic treatment^2. If fasting glucose does not decrease to ≤ 160 mg/dL or 8.9 mmol/L within 21 days under appropriate anti-hyperglycemic treatment^2,3, reduce PIQRAY dose by 1 dose level and follow fasting glucose value specific recommendations.
Grade 3 > 250-500 mg/dL or > 13.9-27.8 mmol/L | Interrupt PIQRAY. Initiate or intensify oral anti-hyperglycemic treatment^2 and consider additional anti-hyperglycemic medications^3 for 1-2 days until hyperglycemia improves, as clinically indicated. Administer intravenous hydration and consider appropriate treatment (e.g., intervention for electrolyte/ketoacidosis/hyperosmolar disturbances). If fasting glucose decreases to ≤ 160 mg/dL or 8.9 mmol/L within 3 to 5 days under appropriate anti-hyperglycemic treatment, resume PIQRAY at 1 lower dose level. If fasting glucose does not decrease to ≤ 160 mg/dL or 8.9 mmol/L within 3 to 5 days under appropriate anti-hyperglycemic treatment, consultation with a physician with expertise in the treatment of hyperglycemia is recommended. If fasting glucose does not decrease to ≤ 160 mg/dL or 8.9 mmol/L within 21 days following appropriate anti-hyperglycemic treatment^2,3, permanently discontinue PIQRAY treatment.
Grade 4 > 500 mg/dL or > 27.8 mmol/L | Interrupt PIQRAY. Initiate or intensify appropriate anti-hyperglycemic treatment^2,3 (administer intravenous hydration and consider appropriate treatment (e.g., intervention for electrolyte/ketoacidosis/hyperosmolar disturbances)), re-check fasting glucose within 24 hours and as clinically indicated. If fasting glucose decreases to ≤ 500 mg/dL or 27.8 mmol/L, follow fasting glucose value-specific recommendations for Grade 3. If fasting glucose is confirmed at > 500 mg/dL or 27.8 mmol/L, permanently discontinue PIQRAY treatment.
Abbreviation: ULN, upper limit of normal.
^1FPG/Fasting Blood Glucose/Grade levels reflect hyperglycemia grading according to Common Terminology Criteria for Adverse Events (CTCAE) Version 4.03.
^2Initiate applicable anti-hyperglycemic medications, including metformin, SGLT2 inhibitors or insulin sensitizers (such as thiazolidinediones or dipeptidyl peptidase-4 inhibitors), and review respective prescribing information for dosing and dose titration recommendations, including local hyperglycemic treatment guidelines. Metformin was recommended in the SOLAR-1 trial with the following guidance: Initiate metformin 500 mg once daily. Based on tolerability, metformin dose may be increased to 500 mg twice daily, followed by 500 mg with breakfast, and 1,000 mg with dinner, followed by further increase to 1,000 mg twice daily if needed [see Warnings and Precautions (5.3)].
^3As recommended in the SOLAR-1 trial, insulin may be used for 1-2 days until hyperglycemia resolves. However, this may not be necessary in the majority of PIQRAY-induced hyperglycemia, given the short half-life of PIQRAY and the expectation of glucose levels normalizing after interruption of PIQRAY.

Diarrhea or Colitis

Table 4: Dose Modification and Management for Diarrhea or Colitis
[see Warnings and Precautions (5.5)]
Grade^1 | Recommendation
Grade 1 | No PIQRAY dose adjustment is required. Initiate appropriate medical therapy and monitor as clinically indicated.
Grade 2 | Interrupt PIQRAY dose until improvement to Grade ≤ 1, then resume PIQRAY at the same dose level. For recurrent Grade ≥ 2, interrupt PIQRAY dose until improvement to Grade ≤ 1, then resume PIQRAY at the next lower dose level. Initiate or intensify appropriate medical therapy and monitor as clinically indicated^2.
Grade 3 | Interrupt PIQRAY dose until improvement to Grade ≤ 1, then resume PIQRAY at the next lower dose level. Initiate or intensify appropriate medical therapy and monitor as clinically indicated^2.
Grade 4 | Permanently discontinue PIQRAY.
^1Grading according to CTCAE Version 5.0.
^2For Grade 2 and 3 colitis, consider additional treatment, such as enteric-acting and/or systemic steroids.

Other Toxicities

Table 5: Dose Modification and Management for Other Toxicities (Excluding Hyperglycemia, Rash and Severe Cutaneous Adverse Reactions, and Diarrhea or Colitis)
Grade^1 | Recommendation
Grade 1 or 2 | No PIQRAY dose adjustment is required. Initiate appropriate medical therapy and monitor as clinically indicated^2,3.
Grade 3 | Interrupt PIQRAY dose until improvement to Grade ≤ 1, then resume PIQRAY at the next lower dose level.
Grade 4 | Permanently discontinue PIQRAY.
^1Grading according to CTCAE Version 5.0.
^2For Grade 2 and 3 pancreatitis, interrupt PIQRAY dose until improvement to Grade < 2 and resume at next lower-dose level. Only one dose reduction is permitted. If toxicity reoccurs, permanently discontinue PIQRAY treatment.
^3For Grade 2 total bilirubin elevation, interrupt PIQRAY dose until improvement to Grade ≤ 1 and resume at the same dose if resolved in ≤ 14 days or resume at the next lower dose level if improved in > 14 days.

Refer to the Full Prescribing Information of fulvestrant for dose modification guidelines in the event of toxicity and for other relevant safety information.

3 DOSAGE FORMS AND STRENGTHS

Tablets: 50 mg, 150 mg, and 200 mg alpelisib

50 mg: Light pink, unscored, round and curved with beveled edges film-coated tablet, imprinted with “L7” on one side and “NVR” on the other side.

150 mg: Pale red, unscored, ovaloid and curved with beveled edges film-coated tablet, imprinted with “UL7” on one side and “NVR” on the other side.

200 mg: Light red, unscored, ovaloid and curved with beveled edges film-coated tablet, imprinted with “YL7” on one side and “NVR” on the other side.

4 CONTRAINDICATIONS

PIQRAY is contraindicated in patients with severe hypersensitivity to it or any of its components [see Warnings and Precautions (5.1)].

5 WARNINGS AND PRECAUTIONS

5.1 Severe Hypersensitivity

Severe hypersensitivity reactions, including anaphylaxis and anaphylactic shock, can occur in patients treated with PIQRAY. Severe hypersensitivity reactions were manifested by symptoms, including, but not limited to, dyspnea, flushing, rash, fever, or tachycardia.

The incidence of Grade 3 and 4 hypersensitivity reactions was 0.7% [see Adverse Reactions (6)].

Angioedema has been reported in the postmarketing setting in patients treated with PIQRAY [see Adverse Reactions (6.2)].

Advise patients of the signs and symptoms of severe hypersensitivity reactions. Permanently discontinue PIQRAY in the event of severe hypersensitivity.

5.2 Severe Cutaneous Adverse Reactions

Severe cutaneous adverse reactions (SCARs), including Stevens-Johnson syndrome (SJS), erythema multiforme (EM), toxic epidermal necrolysis (TEN), and drug reaction with eosinophilia and systemic symptoms (DRESS) can occur in patients treated with PIQRAY.

In the SOLAR-1 study, SJS and EM were reported in 0.4% and 1.1% of the patients, respectively [see Adverse Reactions (6.1)]. Drug reaction with eosinophilia and systemic symptoms (DRESS) was reported in patients treated with PIQRAY in the postmarketing setting [see Adverse Reactions (6.2)].

If signs or symptoms of SCARs occur, interrupt PIQRAY until the etiology of the reaction has been determined. Consultation with a dermatologist is recommended.

If a SCAR is confirmed, permanently discontinue PIQRAY. Do not reintroduce PIQRAY in patients who have experienced previous severe cutaneous adverse reactions during PIQRAY treatment.

If a SCAR is not confirmed, PIQRAY may require dose modifications, topical corticosteroids, or oral antihistamine treatment as described in Table 2 [see Dosage and Administration (2.3)].

Advise patients of the signs and symptoms of SCARs (e.g., a prodrome of fever, flu-like symptoms, mucosal lesions, progressive skin rash, or lymphadenopathy).

5.3 Hyperglycemia

Severe hyperglycemia, in some cases associated with hyperglycemic hyperosmolar non-ketotic syndrome (HHNKS) or ketoacidosis has occurred in patients treated with PIQRAY. Fatal cases of ketoacidosis have occurred in the postmarketing setting.

Hyperglycemia was reported in 65% of patients treated with PIQRAY. Grade 3 (FPG > 250 to 500 mg/dL) and Grade 4 (FPG > 500 mg/dL) hyperglycemia was reported in 33% and 3.9% of patients, respectively. Ketoacidosis was reported in 0.7% of patients (n = 2) treated with PIQRAY.

Among the patients who experienced Grade ≥ 2 (FPG 160 to 250 mg/dL) hyperglycemia, the median time to first occurrence of hyperglycemia was 15 days (range, 5 to 517 days).

In the 187 patients with hyperglycemia, 87% (163/187) were managed with anti-hyperglycemic medication, and 76% (142/187) reported use of metformin as single agent or in combination with other anti-hyperglycemic medication [i.e., insulin, dipeptidyl peptidase-4 (DPP-4) inhibitors, and sulfonylureas]. In patients with Grade ≥ 2 hyperglycemia with at least 1 grade improvement (n = 153), median time to improvement from the first event was 8 days (range, 2 to 65 days).

In all patients with elevated FPG who continued fulvestrant treatment after discontinuing PIQRAY (n = 54), 96% (n = 52) of patients had FPG levels that returned to baseline.

Before initiating treatment with PIQRAY, test fasting plasma glucose (FPG), HbA1c, and optimize blood glucose. After initiating treatment with PIQRAY, monitor fasting glucose (FPG or fasting blood glucose) at least once every week for the first 2 weeks, then at least once every 4 weeks, and as clinically indicated. Monitor HbA1c every 3 months and as clinically indicated. Monitor fasting glucose more frequently for the first few weeks during treatment with PIQRAY in patients with risk factors for hyperglycemia, such as obesity (BMI ≥ 30), elevated FPG, HbA1c at the upper limit of normal or above, use of concomitant systemic corticosteroids, or age ≥ 75 [see Use in Specific Populations (8.5)].

If a patient experiences hyperglycemia after initiating treatment with PIQRAY, monitor fasting glucose as clinically indicated, and at least twice weekly until fasting glucose decreases to normal levels. During treatment with anti-hyperglycemic medication, continue monitoring fasting glucose at least once a week for 8 weeks, followed by once every 2 weeks and as clinically indicated. Consider consultation with a healthcare practitioner with expertise in the treatment of hyperglycemia and counsel patients on lifestyle changes.

The safety of PIQRAY in patients with Type 1 and uncontrolled Type 2 diabetes has not been established as these patients were excluded from the SOLAR-1 trial. Patients with a medical history of controlled Type 2 diabetes were included. Patients with a history of diabetes mellitus may require intensified hyperglycemic treatment. Closely monitor patients with diabetes.

Consider premedication with metformin prior to the initiation of PIQRAY in combination with fulvestrant based on patient risk factors for hyperglycemia, gastrointestinal tolerability, and clinical situation. In the METALLICA study, use of metformin starting 7 days prior to the initiation of PIQRAY appeared to decrease the incidence and severity of hyperglycemia events, but increased the incidence and severity of nausea, vomiting, and diarrhea adverse reactions [see Adverse Reactions (6.1)].

Based on the severity of the hyperglycemia, PIQRAY may require dose interruption, reduction, or discontinuation as described in Table 3 [see Dosage and Administration (2.3)].

Advise patients of the signs and symptoms of hyperglycemia (e.g., excessive thirst, urinating more often than usual or higher amount of urine than usual, or increased appetite with weight loss).

5.4 Pneumonitis

Severe pneumonitis, including acute interstitial pneumonitis and interstitial lung disease, can occur in patients treated with PIQRAY.

Pneumonitis was reported in 1.8% of patients treated with PIQRAY.

In patients who have new or worsening respiratory symptoms or are suspected to have developed pneumonitis, interrupt PIQRAY immediately and evaluate the patient for pneumonitis. Consider a diagnosis of non-infectious pneumonitis in patients presenting with non-specific respiratory signs and symptoms, such as hypoxia, cough, dyspnea, or interstitial infiltrates on radiologic exams and in whom infectious, neoplastic, and other causes have been excluded by means of appropriate investigations.

Permanently discontinue PIQRAY in all patients with confirmed pneumonitis.

Advise patients to immediately report new or worsening respiratory symptoms.

5.5 Diarrhea or Colitis

Severe diarrhea, resulting in dehydration and in some cases in acute kidney injury, can occur in patients treated with PIQRAY. Most patients (58%) experienced diarrhea during treatment with PIQRAY. Grade 3 diarrhea occurred in 7% (n = 19) of patients. Among patients with Grade 2 or 3 diarrhea (n = 71), the median time to onset was 46 days (range, 1 to 442 days).

In clinical trials, 63% of patients who experienced diarrhea required antidiarrheal medications (e.g., loperamide) to manage symptoms. Dose reductions of PIQRAY were required in 6% of patients, and 2.8% of patients permanently discontinued PIQRAY due to diarrhea.

Colitis has been reported in the postmarketing setting in patients treated with PIQRAY [see Adverse Reactions (6.2)].

Monitor patients for diarrhea and additional symptoms of colitis, such as abdominal pain and mucus or blood in stool. Based on the severity of the diarrhea or colitis, PIQRAY may require dose interruption, reduction, or discontinuation as described in Table 4 [see Dosage and Administration (2.3)].

Advise patients to start antidiarrheal treatment, increase oral fluids, and notify their healthcare provider if diarrhea occurs while taking PIQRAY.

Patients with colitis may require additional treatment, such as enteric-acting and/or systemic steroids.

5.6 Embryo-Fetal Toxicity

Based on findings in animals and its mechanism of action, PIQRAY can cause fetal harm when administered to a pregnant woman. In animal reproduction studies, oral administration of alpelisib to pregnant rats and rabbits during organogenesis caused adverse developmental outcomes, including embryo-fetal mortality (post-implantation loss), reduced fetal weights, and increased incidences of fetal malformations at maternal exposures based on area under the curve (AUC) that were ≥ 0.8 times the exposure in humans at the recommended dose of 300 mg/day. Advise pregnant women and females of reproductive potential of the potential risk to a fetus. Advise females of reproductive potential to use effective contraception during treatment with PIQRAY and for 1 week after the last dose. Advise male patients with female partners of reproductive potential to use condoms and effective contraception during treatment with PIQRAY and for 1 week after the last dose [see Use in Specific Populations (8.1, 8.3) and Clinical Pharmacology (12.1)].

Refer to the Full Prescribing Information of fulvestrant for pregnancy and contraception information.

6 ADVERSE REACTIONS

The following adverse reactions are discussed in greater detail in other sections of the labeling:

- Severe Hypersensitivity [see Warnings and Precautions (5.1)]
- Severe Cutaneous Adverse Reactions [see Warnings and Precautions (5.2)]
- Hyperglycemia [see Warnings and Precautions (5.3)]
- Pneumonitis [see Warnings and Precautions (5.4)]
- Diarrhea or Colitis [see Warnings and Precautions (5.5)]

6.1 Clinical Trial Experience

Because clinical trials are conducted under widely varying conditions, adverse reaction rates observed in the clinical trials of a drug cannot be directly compared to rates in the clinical trials of another drug and may not reflect the rates observed in practice.

The safety of PIQRAY was evaluated in a randomized, double-blind, placebo-controlled trial (SOLAR-1) in 571 patients with HR-positive, HER2-negative, advanced or metastatic breast cancer enrolled into two cohorts, with or without a PIK3CA mutation [see Clinical Studies (14)].

Patients received either PIQRAY 300 mg plus fulvestrant (n = 284) or placebo plus fulvestrant (n = 287). Fulvestrant 500 mg was administered intramuscularly on Cycle 1, Day 1 and 15, and then at Day 1 of each 28-day cycle during treatment phase.

Two patients (0.7%) died while on treatment with PIQRAY plus fulvestrant due to causes other than the underlying malignancy. Causes of death included one cardio-respiratory arrest and one second primary malignancy. Neither was suspected to be related to study treatment.

Serious adverse reactions occurred in 35% of patients receiving PIQRAY plus fulvestrant. Serious adverse reactions in > 2% of patients receiving PIQRAY plus fulvestrant included hyperglycemia (10%), rash (3.5%), diarrhea (2.8%), acute kidney injury (2.5%), abdominal pain (2.1%), and anemia (2.1%).

Osteonecrosis of the jaw (ONJ) was reported in 4.2% of patients (12/284) in the PIQRAY plus fulvestrant arm compared to 1.4% of patients (4/287) in the placebo arm. All patients experiencing ONJ had prior or concomitant bisphosphonates or RANK-ligand inhibitor administration.

Among patients receiving PIQRAY plus fulvestrant, 4.6% permanently discontinued both PIQRAY and fulvestrant and 21% permanently discontinued PIQRAY alone, due to adverse reactions. The most frequent adverse reactions leading to treatment discontinuation of PIQRAY in > 2% patients receiving PIQRAY plus fulvestrant were hyperglycemia (6%), rash (4.2%), diarrhea (2.8%), and fatigue (2.5%).

Dose reductions due to adverse reactions occurred in 55% of patients receiving PIQRAY plus fulvestrant. The most frequent adverse reactions leading to dose reduction in > 2% patients receiving PIQRAY plus fulvestrant were hyperglycemia (29%), rash (9%), diarrhea (6%), stomatitis (3.5%), and mucosal inflammation (2.1%).

The most common adverse reactions, including laboratory abnormalities (all grades, incidence ≥ 20%) were glucose increased, creatinine increased, diarrhea, rash, lymphocyte count decreased, gamma-glutamyl transferase (GGT) increased, nausea, alanine aminotransferase (ALT) increased, fatigue, hemoglobin decreased, lipase increased, decreased appetite, stomatitis, vomiting, weight decreased, calcium decreased, glucose decreased, activated partial thromboplastin time (aPTT) prolonged, and alopecia.

Adverse reactions and laboratory abnormalities are listed in Table 6 and Table 7, respectively.

Table 6: Adverse Reactions Occurring in ≥ 10% and ≥ 2% Higher than Placebo Arm in SOLAR-1 (All Grades)
 | PIQRAY plus fulvestrant N = 284 |  | Placebo plus fulvestrant N = 287
Adverse reactions | All Grades | Grade 3-4 | All Grades | Grade 3-4
 | % | % | % | %
Gastrointestinal disorders
Diarrhea | 58 | 7* | 16 | 0.3*
Nausea | 45 | 2.5* | 22 | 0.3*
Stomatitis^1 | 30 | 2.5* | 6 | 0*
Vomiting | 27 | 0.7* | 10 | 0.3*
Abdominal pain^2 | 17 | 1.4* | 11 | 1*
Dyspepsia | 11 | 0* | 6 | 0*
General disorders and administration site conditions
Fatigue^3 | 42 | 5* | 29 | 1*
Mucosal inflammation | 19 | 2.1* | 1 | 0*
Edema peripheral | 15 | 0* | 5 | 0.3*
Pyrexia | 14 | 0.7 | 4.9 | 0.3*
Mucosal dryness^4 | 12 | 0.4* | 4.2 | 0*
Infections and infestations
Urinary tract infection^5 | 10 | 0.7* | 5 | 1*
Investigations
Weight decreased | 27 | 3.9* | 2.1 | 0*
Metabolism and nutrition disorders
Decreased appetite | 36 | 0.7* | 10 | 0.3*
Nervous system disorders
Dysgeusia^6 | 18 | 0.4* | 3.5 | 0*
Headache | 18 | 0.7* | 13 | 0*
Skin and subcutaneous tissue disorders
Rash^7 | 52 | 20* | 7 | 0.3*
Alopecia | 20 | 0* | 2.4 | 0*
Pruritus | 18 | 0.7* | 6 | 0*
Dry skin^8 | 18 | 0.4* | 3.8 | 0*
Grading according to CTCAE Version 4.03.
^1Stomatitis: including stomatitis, aphthous ulcer and mouth ulceration.
^2Abdominal pain: abdominal pain, abdominal pain upper, abdominal pain lower.
^3Fatigue: including fatigue, asthenia.
^4Mucosal dryness: including dry mouth, mucosal dryness, vulvovaginal dryness.
^5Urinary tract infection: including UTI and single case of urosepsis.
^6Dysgeusia: including dysgeusia, ageusia, hypogeusia.
^7Rash: including rash, rash maculo-papular, rash macular, rash generalized, rash papular, rash pruritic.
^8Dry skin: including dry skin, skin fissures, xerosis, xeroderma.
*No Grade 4 adverse reactions were reported.

Among the patients with Grade 2 or 3 rash, the median time to first onset of Grade 2 or 3 rash was 12 days. A subgroup of 86 patients received premedication, including antihistamines, prior to onset of rash. In these patients, rash was reported less frequently than in the overall population, for all grades rash (27% vs 54%), Grade 3 rash (12% vs 20%) and rash leading to permanent discontinuation of PIQRAY (3.5% vs 4.2%). Of the 153 patients who experienced rash, 141 had resolution of the rash.

Table 7: Laboratory Abnormalities Occurring in ≥ 10% of Patients in SOLAR-1
 | PIQRAY plus fulvestrant N = 284 |  | Placebo plus fulvestrant N = 287
Laboratory abnormality | All Grades | Grade 3-4 | All Grades | Grade 3-4
 | % | % | % | %
Hematological parameters
Lymphocyte count decreased | 52 | 8 | 40 | 4.5*
Hemoglobin decreased | 42 | 4.2* | 29 | 1*
Activated partial thromboplastin time (aPTT) prolonged | 21 | 0.7* | 16 | 0.3*
Platelet count decreased | 14 | 1.1 | 6 | 0*
Biochemical parameters
Glucose increased^1 | 79 | 39 | 34 | 1
Creatinine increased | 67 | 2.8* | 25 | 0.7*
Gamma glutamyl transferase (GGT) increased | 52 | 11 | 44 | 10
Alanine aminotransferase (ALT) increased | 44 | 3.5 | 34 | 2.4*
Lipase increased | 42 | 7 | 25 | 6
Calcium (corrected) decreased | 27 | 2.1 | 20 | 1.4
Glucose decreased | 26 | 0.4 | 14 | 0*
Potassium decreased | 14 | 6 | 2.8 | 0.7*
Albumin decreased | 14 | 0* | 8 | 0*
Magnesium decreased | 11 | 0.4* | 4.2 | 0*
^1Glucose increase is an expected laboratory abnormality of PI3K inhibition.
*No Grade 4 laboratory abnormalities were reported.

Metformin Premedication for Hyperglycemia Adverse Reactions

The safety of PIQRAY and endocrine therapy with metformin premedication was evaluated in METALLICA (NCT04300790), a single-arm, two-cohort study in 68 patients with HR-positive, HER2-negative advanced breast cancer harboring PIK3CA mutation(s). The majority of patients (93%) received fulvestrant as endocrine therapy during the study.
Cohort A enrolled patients with normal glycemic status (FPG < 100 mg/dl [< 5.6 mmol/L] and HbA1c < 5.7%) and Cohort B enrolled patients with impaired glycemic status (FPG 100–140 mg/dL [5.6–7.8 mmol/L] or HbA1c 5.7%–6.4%).

Metformin was administered beginning 7 days prior to treatment with PIQRAY. On Day 1 to Day 3, metformin 500 mg twice daily was administered orally and then increased up to 1,000 mg twice daily based on tolerability.

Hyperglycemia adverse reactions occurred in 33% (16/48) and 70% (14/20 patients) in Cohort A and Cohort B, respectively. Grade 3-4 hyperglycemia occurred in 2.1% (1/48) of patients in Cohort A and 15% (3/20) of patients in Cohort B. The incidence of nausea, vomiting, and diarrhea adverse reactions, including Grade 3 diarrhea, increases with metformin premedication [see Warnings and Precautions (5.3)].

Serious adverse reactions occurred in 22% of patients in the METALLICA study and serious adverse reactions ≥ 2% included diarrhea (3%), rash (3%) and vomiting (3%).

The most common Grade 3-4 adverse reactions (≥ 5%) were rash (16%), diarrhea (13%), and hyperglycemia (6%).

Permanent discontinuation of PIQRAY due to adverse reactions in the METALLICA study occurred in 19% of patients, and dose modification or interruption of PIQRAY due to adverse reactions occurred in 56% of patients, of which 28% were dose reductions.

The most common adverse reactions (≥ 30%) in the METALLICA study were diarrhea (68%), nausea (68%), fatigue (46%), hyperglycemia (44%), rash (38%), and vomiting (34%).

6.2 Postmarketing Experience

The following adverse reactions have been identified during post approval use of PIQRAY. Because these reactions are reported voluntarily from a population of uncertain size, it is not always possible to reliably estimate their frequency or establish a causal relationship to drug exposure.

Eye disorders: Uveitis

Gastrointestinal disorders: Colitis

Metabolism and nutrition disorders: Hyperglycemic hyperosmolar nonketotic syndrome (HHNKS).

Skin and subcutaneous tissue disorders: Angioedema, Drug reaction with eosinophilia and systemic symptoms (DRESS).

7 DRUG INTERACTIONS

7.1 Effect of Other Drugs on PIQRAY

CYP3A4 Inducer

Coadministration of PIQRAY with a strong CYP3A4 inducer decreases alpelisib concentration [see Clinical Pharmacology (12.3)], which may reduce alpelisib efficacy. Avoid concomitant use of strong CYP3A4 inducers and consider an alternative concomitant drug with no or minimal potential to induce CYP3A4.

Breast Cancer Resistance Protein Inhibitors

Coadministration of PIQRAY with a breast cancer resistance protein (BCRP) inhibitor may increase alpelisib concentration [see Clinical Pharmacology (12.3)], which may increase the risk of toxicities. Avoid the use of BCRP inhibitors in patients treated with PIQRAY. If unable to use alternative drugs, when PIQRAY is used in combination with BCRP inhibitors, closely monitor for increased adverse reactions.

8 USE IN SPECIFIC POPULATIONS

8.1 Pregnancy

Risk Summary

PIQRAY is used in combination with fulvestrant. Refer to the Full Prescribing Information of fulvestrant for pregnancy information.

Based on animal data and mechanism of action, PIQRAY can cause fetal harm when administered to a pregnant woman [see Clinical Pharmacology (12.1)]. There are no available data in pregnant women to inform the drug-associated risk. In animal reproduction studies, oral administration of alpelisib to pregnant rats and rabbits during organogenesis caused adverse developmental outcomes, including embryo-fetal mortality (post-implantation loss), reduced fetal weights, and increased incidences of fetal malformations at maternal exposures ≥ 0.8 times the exposure in humans based on AUC at the recommended dose of 300 mg/day (see Data). Advise pregnant women and females of reproductive potential of the potential risk to a fetus.

The estimated background risk of major birth defects and miscarriage for the indicated population is unknown. However, the estimated background risk of major birth defects is 2% to 4% and of miscarriage is 15% to 20% of clinically recognized pregnancies in the U.S. general population.

Data

Animal Data

In embryo-fetal development studies in rats and rabbits, pregnant animals received oral doses of alpelisib up to 30 mg/kg/day during the period of organogenesis.

In rats, oral administration of alpelisib resulted in maternal toxicity (body weight loss, low food consumption) and no viable fetuses (post-implantation loss) at 30 mg/kg/day (approximately 3 times the exposure in humans at the recommended dose of 300 mg/day based on AUC). At a dose of 10 mg/kg/day (approximately 0.8 times the exposure in humans at the recommended dose of 300 mg/day based on AUC), toxicities included reduced fetal weight and increased incidences of skeletal malformations (bent scapula and thickened or bent long bones) and fetal variations (enlarged brain ventricle, decreased bone ossification).

In a pilot embryo-fetal development study in rabbits, a dose of 30 mg/kg/day resulted in no viable fetuses (post-implantation loss). Doses ≥ 15 mg/kg/day resulted in increased embryo-fetal deaths, reduced fetal weights, and malformations, mostly related to the tail and head. At 15 mg/kg/day in rabbits, the maternal exposure was approximately 5 times the exposure achieved at the recommended human dose of 300 mg/day based on AUC.

8.2 Lactation

PIQRAY is used in combination with fulvestrant. Refer to the Full Prescribing Information of fulvestrant for lactation information.

There is no data on the presence of alpelisib in human milk, its effects on milk production, or the breastfed child. Because of the potential for serious adverse reactions in the breastfed child, advise lactating women to not breastfeed during treatment with PIQRAY and for 1 week after the last dose.

8.3 Females and Males of Reproductive Potential

PIQRAY is used in combination with fulvestrant. Refer to the Full Prescribing Information of fulvestrant for contraception and infertility information.

Pregnancy Testing

Verify the pregnancy status in females of reproductive potential prior to initiating PIQRAY.

Contraception

Females

PIQRAY can cause fetal harm when administered to a pregnant woman [see Use in Specific Populations (8.1)]. Advise females of reproductive potential to use effective contraception during treatment with PIQRAY and for 1 week after the last dose.

Males

Advise male patients with female partners of reproductive potential to use condoms and effective contraception during treatment with PIQRAY and for 1 week after the last dose.

Infertility

Based on findings from animal studies, PIQRAY may impair fertility in males and females of reproductive potential [see Nonclinical Toxicology (13.1)].

8.4 Pediatric Use

The safety and efficacy of PIQRAY in pediatric patients have not been established.

8.5 Geriatric Use

Of 284 patients who received PIQRAY in the SOLAR-1 trial, 117 patients were ≥ 65 years of age and 34 patients were ≥ 75 years of age. In patients treated with PIQRAY plus fulvestrant, there was a higher incidence of Grade 3-4 hyperglycemia in patients ≥ 65 years of age (44%) compared to patients < 65 years of age (32%). No overall differences in effectiveness of PIQRAY were observed between patients ≥ 65 years of age compared to younger patients. There are an insufficient number of patients ≥ 75 years of age to assess whether there are differences in safety or effectiveness. However, in the SOLAR-1 trial, an increase in the hyperglycemia adverse reactions (74% vs 66%) and Grade 3-4 (56% vs 36%) hyperglycemia were observed in patients ≥ 75 years of age compared to patients < 75 years of age, respectively [see Warnings and Precautions (5.3)].

8.6 Renal Impairment

The effect of severe renal impairment (CLcr < 30 mL/min) on alpelisib pharmacokinetics is unknown [see Clinical Pharmacology (12.3)].

No dose adjustment is recommended for patients with mild to moderate renal impairment (CLcr 30 to < 90 mL/min).

10 OVERDOSAGE

There is limited experience of overdose with PIQRAY in clinical trials. In the clinical studies, PIQRAY was administered at doses up to 450 mg once daily.

In cases where accidental overdosage of PIQRAY was reported in the clinical studies, the adverse reactions associated with the overdose were consistent with the known safety profile of PIQRAY and included hyperglycemia, nausea, asthenia, and rash.

Initiate general symptomatic and supportive measures in all cases of overdosage where necessary. There is no known antidote for PIQRAY.

11 DESCRIPTION

PIQRAY (alpelisib) is a kinase inhibitor. The chemical name of alpelisib is (2S)-N^1-[4-Methyl-5-[2-(2,2,2-trifluoro-1,1-dimethylethyl)-4-pyridinyl]-2-thiazolyl]-1,2-pyrrolidinedicarboxamide. Alpelisib is a white to almost white powder. The molecular formula for alpelisib is C19H22F3N5O2S and the relative molecular mass is 441.47 g/mol. The chemical structure of alpelisib is shown below:

PIQRAY film-coated tablets are supplied for oral administration with three strengths that contain 50 mg, 150 mg and 200 mg of alpelisib. The tablets also contain hypromellose, magnesium stearate, mannitol, microcrystalline cellulose, and sodium starch glycolate. The film-coating contains hypromellose, iron oxide black, iron oxide red, macrogol/polyethylene glycol (PEG) 4000, talc, and titanium dioxide.

12 CLINICAL PHARMACOLOGY

12.1 Mechanism of Action

Alpelisib is an inhibitor of phosphatidylinositol-3-kinase (PI3K) with inhibitory activity predominantly against PI3Kα. Gain-of-function mutations in the gene encoding the catalytic α-subunit of PI3K (PIK3CA) lead to activation of PI3Kα and Akt-signaling, cellular transformation and the generation of tumors in in vitro and in vivo models.

In breast cancer cell lines, alpelisib inhibited the phosphorylation of PI3K downstream targets, including Akt and showed activity in cell lines harboring a PIK3CA mutation. In vivo, alpelisib inhibited the PI3K/Akt signaling pathway and reduced tumor growth in xenograft models, including models of breast cancer.

PI3K inhibition by alpelisib treatment has been shown to induce an increase in estrogen receptor (ER) transcription in breast cancer cells. The combination of alpelisib and fulvestrant demonstrated increased anti-tumor activity compared to either treatment alone in xenograft models derived from ER-positive, PIK3CA mutated breast cancer cell lines.

12.2 Pharmacodynamics

Cardiac Electrophysiology

Serial ECGs were collected following a single dose and at steady-state to evaluate the effect of alpelisib on the QTcF interval in patients with advanced cancer. An analysis of clinical ECG data demonstrates the absence of a large effect (i.e., > 20 ms) on QTcF prolongation at the recommended 300 mg dose with or without fulvestrant.

12.3 Pharmacokinetics

The pharmacokinetics of alpelisib has been studied in healthy subjects and adult patients with solid tumors. Steady-state alpelisib maximum plasma concentration (Cmax) and AUC increased proportionally over the dose range of 30 mg to 450 mg (0.1 to 1.5 times the approved recommended dosage) under fed conditions. The mean accumulation of alpelisib is 1.3 to 1.5 and steady-state plasma concentrations are reached within 3 days following daily dosage. In adult patients who received PIQRAY 300 mg once daily in the SOLAR-1 trial, population approach derived mean steady-state alpelisib [coefficient of variation (CV%)] for Cmax was 2480 (23%) ng/mL and AUC0-24hr was 33224 (21%) ng*h/mL.

Absorption

The median time to reach peak plasma concentration (Tmax) ranged between 2.0 to 4.0 hours.

Effect of food

A high-fat high-calorie meal (985 calories with 58.1 g of fat) increased alpelisib AUC by 73% and Cmax by 84%, and a low-fat low-calorie meal (334 calories with 8.7 g of fat) increased alpelisib AUC by 77% and Cmax by 145% following a single dose of PIQRAY. No clinically significant differences in alpelisib AUC were observed between low-fat low-calorie and high-fat high-calorie meals.

Distribution

The mean (% CV) apparent volume of distribution of alpelisib at steady-state is predicted to be 114 L (46%). Protein binding of alpelisib is 89% and is independent of concentration.

Elimination

The half-life of alpelisib is predicted to be 8 to 9 hours. The mean (% CV) clearance of alpelisib is predicted to be 9.2 L/hr (21%) under fed conditions.

Metabolism

Alpelisib is primarily metabolized by chemical and enzymatic hydrolysis to form its metabolite BZG791 and followed by CYP3A4 mediated hydroxylation.

Excretion

Following a single oral dose of 400 mg radiolabeled alpelisib under fasted condition, 81% of the administered dose was recovered in feces (36% unchanged, 32% BZG791) and 14% (2% unchanged, 7.1% BZG791) in urine. CYP3A4-mediated metabolites (12%) and glucuronides amounted to approximately 15% of the dose.

Specific Populations

No clinically significant differences in the pharmacokinetics of alpelisib were predicted based on age (21 to 87 years), sex, race/ethnicity (Japanese or Caucasian), body weight (37 to 181 kg), mild to moderate renal impairment (CLcr 30 to < 90 mL/min based on the Cockcroft-Gault formula), or mild to severe hepatic impairment (Child-Pugh Class A, B, and C). The effect of severe renal impairment (CLcr < 30 mL/min) on the pharmacokinetics of alpelisib is unknown.

Drug Interaction Studies

Clinical Studies

Acid Reducing Agents: PIQRAY can be coadministered with acid reducing agents, since PIQRAY should be taken with food. Food exhibited a more pronounced effect on the solubility of alpelisib than the effect of gastric pH value.

Coadministration of the H2 receptor antagonist ranitidine in combination with a single 300 mg oral dose of alpelisib decreased the absorption and overall exposure of alpelisib. In the presence of a low-fat low-calorie meal, AUC was decreased on average by 21% and Cmax by 36% with ranitidine. Under the fasted state, AUC was decreased on average by 30% and Cmax by 51% with ranitidine.

CYP3A4, CYP2C8, CYP2C9, CYP2C19 and CYP2B6 Substrates: Coadministration of repeated doses of alpelisib 300 mg with a single-dose of sensitive substrates of CYP3A4 (midazolam), CYP2C8 (repaglinide), CYP2C9 (warfarin), CYP2C19 (omeprazole) and CYP2B6 (bupropion), administered as a cocktail did not show clinically significant pharmacokinetic interactions. No clinically significant differences in pharmacokinetics of everolimus (a substrate of CYP3A4 and P-gp) were observed when coadministered with alpelisib.

Effect of CYP3A4 Inducers on Alpelisib: Coadministration of repeat doses of rifampin (a strong CYP3A4 inducer) with a single 300 mg dose of alpelisib decreased alpelisib Cmax by 38% and AUC by 57%, respectively. Coadministration of rifampin with repeat doses of 300 mg alpelisib decreased alpelisib Cmax by 59% and AUC by 74%, respectively.

Model-Informed Approaches

Coadministration of repeat doses of ketoconazole (a strong CYP3A4 inhibitor) with a single 300 mg dose of alpelisib is expected to increase alpelisib AUC by 37% or less.

Coadministration of repeat doses of efavirenz (a moderate CYP3A4 inducer) with a single 300 mg dose of alpelisib is expected to decrease alpelisib AUC by 30% or less.

In Vitro Studies

Effect of Transporter on Alpelisib: Alpelisib is a substrate of BCRP.

Effect of Alpelisib on Transporters: Alpelisib is an inhibitor of P-gp. Alpelisib has a low potential to inhibit BCRP, MRP2, BSEP, OATP1B1, OATP1B3, OCT1, OAT1, OAT3, OCT2, MATE1, and MATE2K at clinically relevant concentrations.

13 NONCLINICAL TOXICOLOGY

13.1 Carcinogenesis, Mutagenesis, Impairment of Fertility

Carcinogenicity studies have not been conducted with alpelisib.

Alpelisib was not mutagenic in an in vitro bacterial reverse mutation (Ames) assay, or aneugenic or clastogenic in human cell micronucleus and chromosome aberration tests. Alpelisib was not genotoxic in an in vivo rat micronucleus test.

In a fertility and early embryonic development study in rats, female animals were administered alpelisib at doses of 3, 10, and 20 mg/kg/day orally. Animals were dosed for 4 weeks prior to pairing, during the mating period, and up to Gestation Day 6. At a dose of 20 mg/kg/day (approximately 1.7 times the exposure in humans at the recommended dose of 300 mg based on AUC), alpelisib increased pre- and post-implantation losses, leading to reduced numbers of implantation sites and live embryos. In a repeated-dose toxicity study in rats, adverse effects in female reproductive organs included vaginal atrophy and estrous cycle variations in rats at doses ≥ 6 mg/kg/day (approximately 0.6 times the exposure in humans at the recommended dose of 300 mg/day based on AUC).

In a male fertility study, alpelisib administered orally at doses of 3, 10, and 20 mg/kg/day for up to 99 days (10-weeks prior to pairing, during mating period and continuing during post-pairing) to male rats, resulted in reduced weights of seminal vesicles and prostate, which correlated with atrophy and/or reduced secretion in prostate and seminal vesicles at ≥ 10 mg/kg/day (approximately 0.8 times the exposure in humans at the recommended dose of 300 mg based on AUC). No adverse effects on male fertility parameters were observed at doses up to 20 mg/kg/day.

14 CLINICAL STUDIES

SOLAR-1 (NCT02437318) was a randomized, double-blind, placebo-controlled trial of PIQRAY plus fulvestrant versus placebo plus fulvestrant in 572 patients with HR-positive, HER2-negative, advanced or metastatic breast cancer whose disease had progressed or recurred on or after an aromatase inhibitor-based treatment (with or without CDK4/6 combination). Patients were excluded if they had inflammatory breast cancer, diabetes mellitus Type 1 or uncontrolled Type 2, or pneumonitis. Randomization was stratified by presence of lung and/or liver metastasis and previous treatment with CDK4/6 inhibitor(s). Overall, 60% of enrolled patients had tumors with one or more PIK3CA mutations in tissue, 50% had liver/lung metastases, and 6% had previously been treated with a CDK4/6 inhibitor.

There were 341 patients enrolled by tumor tissue in the cohort with a PIK3CA mutation and 231 enrolled in the cohort without a PIK3CA mutation. Of the 341 patients in the cohort with a PIK3CA mutation, 336 (99%) patients had one or more PIK3CA mutations confirmed in tumor tissue using the FDA-approved therascreen® PIK3CA RGQ PCR Kit. Out of the 336 patients with PIK3CA mutations confirmed in tumor tissue, 19 patients had no plasma specimen available for testing with the FDA-approved therascreen® PIK3CA RGQ PCR Kit. Of the remaining 317 patients with PIK3CA mutations confirmed in tumor tissue, 177 patients (56%) had PIK3CA mutations identified in plasma specimen, and 140 patients (44%) did not have PIK3CA mutations identified in plasma specimen.

Patients received either PIQRAY (300 mg) or placebo orally once daily on a continuous basis, plus fulvestrant (500 mg) administered intramuscularly on Cycle 1, Days 1 and 15, and then on Day 1 of every 28-day cycle. Patients received treatment until radiographic disease progression or unacceptable toxicity. Tumor assessments were performed every 8 weeks for the first 18 months and every 12 weeks thereafter.

The median age of patients was 63 years (range, 25 to 92). Most patients were women (99.8%), and most patients were white (66%), followed by Asian (22%), Other/Unknown (10%), black or African American (1.4%), and American Indian or Alaskan Native (0.9%). Baseline ECOG performance status was 0 (68%) or 1 (32%).

Patient demographics for those with PIK3CA-mutated tumors were generally representative of the broader study population. The median duration of exposure to PIQRAY plus fulvestrant was 8.2 months with 59% of patients exposed for > 6 months.

The majority of patients (98%) received prior hormonal therapy as the last treatment (48% metastatic setting, 52% adjuvant setting). Primary endocrine resistance, defined as relapsed within 24 months on adjuvant endocrine therapy or progression within 6 months on endocrine therapy for advanced disease, was observed in 13% of patients and secondary endocrine resistance, defined as relapsed after 24 months on adjuvant endocrine therapy, relapsed within 12 months of the end of adjuvant endocrine therapy, or progression after 6 months on endocrine therapy for advanced disease, was observed in 72% of patients.

The major efficacy outcome was investigator-assessed progression-free survival (PFS) in the cohort with a PIK3CA mutation per Response Evaluation Criteria in Solid Tumors (RECIST) v1.1. Additional efficacy outcome measures were overall response rate (ORR) and overall survival (OS) in the cohort with a PIK3CA mutation.

The results from the investigator-assessed PFS and ORR for the cohort with a PIK3CA mutation in tumor tissue are presented in Table 8, and Figure 1. Investigator-assessed PFS results for the cohort with a PIK3CA mutation were supported by consistent results from a blinded independent review committee (BIRC) assessment. Similar results were seen in patients with tissue or plasma PIK3CA mutations. At the pre-specified final OS analysis, there was no significant difference in OS between the PIQRAY plus fulvestrant arm and the placebo plus fulvestrant arm (hazard ratio [HR] = 0.86, 95% CI: 0.64, 1.15).

No benefit was observed in patients whose tumors did not have a PIK3CA tissue mutation (PFS: HR = 0.85, 95% CI: 0.58, 1.25; OS: HR = 0.92, 95% CI: 0.65, 1.29).

Table 8: Efficacy Results in SOLAR-1 (Per Investigator Assessment of Patients with a PIK3CA Tumor Mutation)
 | PIQRAY plus fulvestrant | Placebo plus fulvestrant
Progression-free survival | N = 169 | N = 172
Number of PFS events – n (%) | 103 (61) | 129 (75)
Median PFS months (95% CI) | 11.0 (7.5, 14.5) | 5.7 (3.7, 7.4)
Hazard ratio (95% CI) | 0.65 (0.50, 0.85)
p-value^1 | 0.0013
Overall response rate | N = 126 | N = 136
ORR^2 (95% CI) | 35.7 (27.4, 44.7) | 16.2 (10.4, 23.5)
Abbreviation: CI, confidence interval.
^1p-value obtained from the two-sided stratified log-rank test, stratified by prior CDK4/6 inhibitor usage and presence of lung/liver metastases. P-value was compared to prespecified Haybittle-Peto efficacy boundary (two-sided p ≤ 0.0398).
^2ORR = percentage of patients with confirmed complete response or partial response with measurable disease at baseline.

Figure 1: Progression Free Survival in SOLAR-1 (Per Investigator Assessment of Patients with a PIK3CA Tumor Mutation)

16 HOW SUPPLIED/STORAGE AND HANDLING

PIQRAY (alpelisib) 50 mg, 150 mg, and 200 mg film-coated tablets [see Dosage Forms and Strengths (3)].

Daily dose | Each carton contains | Each blister pack contains | NDC
300 mg daily dose | 2 blister packs (56 tablets total) | A 14-day supply of 28 tablets (28 tablets, 150 mg alpelisib per tablet) | NDC 0078-0708-02
250 mg daily dose | 2 blister packs (56 tablets total) | A 14-day supply of 28 tablets (14 tablets, 200 mg alpelisib per tablet and 14 tablets, 50 mg alpelisib per tablet) | NDC 0078-0715-02
200 mg daily dose | 1 blister pack (28 tablets total) | A 28-day supply of 28 tablets (28 tablets, 200 mg alpelisib per tablet) | NDC 0078-0701-84

Store at 20°C to 25°C (68°F to 77°F), excursions permitted between 15°C and 30°C (59°F and 86°F) [see USP Controlled Room Temperature].

17 PATIENT COUNSELING INFORMATION

Advise the patient to read the FDA-approved patient labeling (Patient Information).

Severe Hypersensitivity

Inform patients of the signs and symptoms of hypersensitivity. Advise patients to contact their healthcare provider immediately for signs and symptoms of hypersensitivity [see Warnings and Precautions (5.1)].

Severe Cutaneous Adverse Reactions

Inform patients of the signs and symptoms of severe cutaneous adverse reactions (SCARs). Advise patients to contact their healthcare provider immediately for signs and symptoms of SCARs [see Warnings and Precautions (5.2)].

Hyperglycemia

Advise patients that PIQRAY may cause hyperglycemia and the need to monitor fasting blood glucose periodically during therapy. Advise patients to contact their healthcare provider immediately for signs and symptoms of hyperglycemia [see Warnings and Precautions (5.3)].

Pneumonitis

Inform patients that PIQRAY may cause pneumonitis and to immediately contact their healthcare provider if they experience respiratory problems [see Warnings and Precautions (5.4)].

Diarrhea or Colitis

Advise patients that PIQRAY may cause diarrhea, which may be severe, and to start antidiarrheal treatment, increase oral fluids, and notify their healthcare provider if diarrhea occurs while taking PIQRAY [see Warnings and Precautions (5.5)].

Advise patients that PIQRAY may cause colitis and to notify their healthcare provider immediately of any symptoms of colitis, such as abdominal pain and mucus or blood in stool, while taking PIQRAY [see Warnings and Precautions (5.5)].

Uveitis

Advise patients to contact their healthcare provider immediately for signs and symptoms of uveitis [see Adverse Reactions (6.2)].

Embryo-Fetal Toxicity

- Inform pregnant women and females of reproductive potential of the potential risk to a fetus. Advise females to inform their healthcare provider of a known or suspected pregnancy [see Warnings and Precautions (5.6) and Use in Specific Populations (8.1)].
- Advise females of reproductive potential to use effective contraception during treatment with PIQRAY and for 1 week after the last dose [see Use in Specific Populations (8.3)].
- Advise male patients with female partners of reproductive potential to use condoms and effective contraception during treatment with PIQRAY and for 1 week after the last dose [see Use in Specific Populations (8.3)].
- Refer to the Full Prescribing Information of fulvestrant for pregnancy and contraception information.

Lactation

Advise women not to breastfeed during treatment with PIQRAY and for 1 week after the last dose [see Use in Specific Populations (8.2)]. Refer to the Full Prescribing Information of fulvestrant for lactation information.

Infertility

Advise males and females of reproductive potential that PIQRAY may impair fertility [see Use in Specific Populations (8.3)]. Refer to the Full Prescribing Information of fulvestrant for infertility information.

Drug Interactions

Advise patients to avoid the use of strong CYP3A4 inducers in patients treated with PIQRAY. Advise patients to avoid the use of BCRP inhibitors while taking PIQRAY. If unable to use alternative drugs, closely monitor for increased adverse reactions. No dose adjustment is required when coadministering PIQRAY with CYP3A4, CYP2C8, CYP2C9, CYP2C19 and CYP2B6 substrates [see Drug Interactions (7.1, 7.2)].

Dosing

- Instruct patients to take PIQRAY at approximately the same time each day and to swallow the tablet(s) whole (tablets should not be chewed, crushed, or split prior to swallowing) [see Dosage and Administration (2.2)].
- Advise patients to take PIQRAY with food [see Clinical Pharmacology (12.3)].
- Instruct patients that if a dose of PIQRAY is missed, it can be taken with food within 9 hours after the time it is usually taken. After more than 9 hours, skip the dose for that day. The next day, take PIQRAY at the usual time. Instruct patients not to take 2 doses to make up for a missed dose.
- Instruct patients that if they vomit after taking the dose of PIQRAY, they should not take an additional dose on that day, and to resume the usual dosing schedule the next day at the usual time [see Dosage and Administration (2.2)].

Distributed by:
Novartis Pharmaceuticals Corporation
East Hanover, New Jersey 07936

© Novartis

T2024-03

PATIENT INFORMATION
PIQRAY® (pik' raye)
(alpelisib)
tablets, for oral use

Important: PIQRAY is used with fulvestrant. You should also read the Patient Information that comes with fulvestrant.

What is PIQRAY?
PIQRAY is a prescription medicine used in combination with the medicine fulvestrant to treat adults who have hormone receptor (HR)-positive, human epidermal growth factor receptor 2 (HER2)-negative breast cancer, with an abnormal phosphatidylinositol-3-kinase catalytic subunit alpha (PIK3CA) gene, that has progressed or spread to other parts of the body (metastatic) while on or after endocrine therapy.
Your healthcare provider will test your cancer for an abnormal “PIK3CA” gene to make sure that PIQRAY is right for you.
It is not known if PIQRAY is safe and effective in children.

Do not take PIQRAY if you have had a severe allergic reaction to PIQRAY or are allergic to any of the ingredients in PIQRAY.

- See the end of this Patient Information leaflet for a complete list of the ingredients in PIQRAY.
- See “What are the possible side effects of PIQRAY?” for signs and symptoms of severe allergic reactions.

Before you take PIQRAY, tell your healthcare provider about all of your medical conditions, including if you:

- have a history of diabetes or high levels of sugar in your blood
- have a history of skin rash, redness of skin, blistering of the lips, eyes or mouth, or skin peeling
- are pregnant or plan to become pregnant. PIQRAY can harm your unborn baby.
  Females who are able to become pregnant:
  - Your healthcare provider will check to see if you are pregnant before you start treatment with PIQRAY.
  - You should use effective birth control (contraception) during treatment with PIQRAY and for 1 week after the last dose.
  - Talk to your healthcare provider about birth control methods that may be right for you during this time.
  - If you become pregnant or think you are pregnant, tell your healthcare provider right away.
  Males with female partners who are able to become pregnant:
  - You should use condoms and effective birth control during treatment with PIQRAY and for 1 week after the last dose.
  - If your female partner becomes pregnant, tell your healthcare provider right away.
- are breastfeeding or plan to breastfeed. It is not known if PIQRAY passes into your breast milk. Do not breastfeed during treatment with PIQRAY and for 1 week after the last dose. Talk to your healthcare provider about the best way to feed your baby during treatment.

Tell your healthcare provider about all of the medicines you take, including prescription and over-the-counter medicines, vitamins, and herbal supplements. Taking PIQRAY with other medicines may affect the way PIQRAY works and may cause side effects. Know the medicines you take. Keep a list of them to show your healthcare provider or pharmacist when you get a new medicine.

How should I take PIQRAY?

- Take PIQRAY exactly as your healthcare provider tells you.
- Do not change your dose or stop taking PIQRAY unless your healthcare provider tells you.
- Take PIQRAY 1 time each day, at about the same time each day.
- Take PIQRAY with food.
- Swallow PIQRAY tablets whole. Do not chew, crush or split the tablets.
- Do not take any PIQRAY tablets that are broken, cracked, or that look damaged.
- If you miss a dose of PIQRAY, you may still take it with food up to 9 hours after the time you usually take it. If it has been more than 9 hours after you usually take your dose, skip the dose for that day. The next day, take the dose at your usual time. Do not take 2 doses to make up for a missed dose.
- If you vomit after taking a dose of PIQRAY, do not take another dose on that day. Take your next dose at your usual time.
- If you take too much PIQRAY, call your healthcare provider or go to the nearest hospital emergency room right away.

What are the possible side effects of PIQRAY?
PIQRAY may cause serious side effects, including:

- Severe allergic reactions. Tell your healthcare provider or get medical help right away if you have trouble breathing, swelling of the face or throat, flushing, rash, fever, or fast heart rate during treatment with PIQRAY.
- Severe skin reactions. Tell your healthcare provider or get medical help right away if you get severe rash or rash that keeps getting worse, reddened skin, flu-like symptoms, blistering of the lips, eyes or mouth, blisters on the skin or skin peeling, and swollen glands, with or without fever.
- High blood sugar levels (hyperglycemia). Hyperglycemia is common with PIQRAY and may be severe. Your healthcare provider will check your blood sugar levels and may give you a medicine called metformin before you start treatment with PIQRAY. Your healthcare provider will monitor your blood sugar levels during treatment and may monitor your blood sugar levels more often if you have a history of Type 2 diabetes. Tell your healthcare provider right away if you develop symptoms of hyperglycemia, including:

◦ excessive thirst
◦ dry mouth
◦ more frequent urination than usual or a higher amount of urine than normal
◦ increased appetite with weight loss

◦ confusion
◦ nausea
◦ vomiting
◦ fruity odor on breath
◦ difficulty breathing
◦ dry or flushed skin

- Lung problems (pneumonitis). Tell your healthcare provider right away if you develop new or worsening symptoms of lung problems, including:

◦ shortness of breath or trouble breathing

◦ cough
◦ chest pain

- Diarrhea or colitis (inflammation of your intestines). Diarrhea is common with PIQRAY and may be severe. Severe diarrhea can lead to the loss of too much body water (dehydration) and kidney injury. Tell your healthcare provider right away if you develop diarrhea, stomach-area (abdominal) pain, or see mucus or blood in your stool during treatment with PIQRAY. Your healthcare provider may tell you to drink more fluids or take medicines to treat diarrhea or colitis.

Your healthcare provider may tell you to decrease your dose, temporarily stop your treatment, or completely stop your treatment with PIQRAY if you get certain serious side effects.

The most common side effects of PIQRAY when used with fulvestrant include:

• rash
• nausea
• tiredness and weakness

• decreased appetite
• mouth sores
• vomiting

• weight loss
• hair loss
• changes in certain blood tests

Tell your healthcare provider right away if you develop any changes in your vision, eye pain, sensitivity to light, or if your eyes look different.
PIQRAY may affect fertility in males and in females who are able to become pregnant. Talk to your healthcare provider if this is a concern for you. These are not all of the possible side effects of PIQRAY.
Call your doctor for medical advice about side effects. You may report side effects to FDA at 1-800-FDA-1088.

How should I store PIQRAY?
Store PIQRAY at room temperature between 68°F to 77°F (20°C to 25°C).
Keep PIQRAY and all medicines out of the reach of children.

General information about the safe and effective use of PIQRAY.
Medicines are sometimes prescribed for purposes other than those listed in a Patient Information leaflet. Do not use PIQRAY for a condition for which it was not prescribed. Do not give PIQRAY to other people, even if they have the same symptoms that you have. It may harm them. You can ask your pharmacist or healthcare provider for more information about PIQRAY that is written for health professionals.

What are the ingredients in PIQRAY?
Active ingredient: alpelisib
Inactive ingredients: hypromellose, magnesium stearate, mannitol, microcrystalline cellulose, and sodium starch glycolate. The film-coating contains hypromellose, iron oxide black, iron oxide red, macrogol/polyethylene glycol (PEG) 4000, talc, and titanium dioxide.
Distributed by: Novartis Pharmaceuticals Corporation, East Hanover, New Jersey 07936
© Novartis
For more information, go to www.PIQRAY.com or call 1-888-669-6682.

This Patient Information has been approved by the U.S. Food and Drug Administration.

Revised: February 2025

T2025-03

PRINCIPAL DISPLAY PANEL

NDC 0078-0708-02

PIQRAY®

(alpelisib) tablets

300 mg daily dose

Take two 150 mg tablets once daily

Rx only

Usual Dosage: Take two 150 mg tablets once daily with food.
Swallow tablets whole. DO NOT chew, crush, or split tablets.
See prescribing information for complete dosage information.

28-Day Supply (56 Tablets)

Contains: Two 14-day blister packs each containing 28 tablets (56 tablets total)

NOVARTIS

PRINCIPAL DISPLAY PANEL

NDC 0078-0715-02

PIQRAY®

(alpelisib) tablets

250 mg daily dose

Take one 200 mg tablet and one 50 mg tablet once daily

Rx only

Usual Dosage: Take one 200 mg tablet and one 50 mg tablet once daily
with food. Swallow tablets whole. DO NOT chew, crush, or split tablets.
See prescribing information for complete dosage information.

28-Day Supply (56 Tablets)

Contains: Two 14-day blister packs each containing 28 tablets (56 tablets total)

200 mg
14 tablets per pack

50 mg
14 tablets per pack

NOVARTIS

PRINCIPAL DISPLAY PANEL

NDC 0078-0701-84

PIQRAY®

(alpelisib) tablets

200 mg daily dose

Take one 200 mg tablet once daily

Rx only

Usual Dosage: Take one 200 mg tablet once daily with food.
Swallow tablets whole. DO NOT chew, crush, or split tablets.
See prescribing information for complete dosage information.

28-Day Supply

Contains: One blister pack containing 28 tablets

NOVARTIS